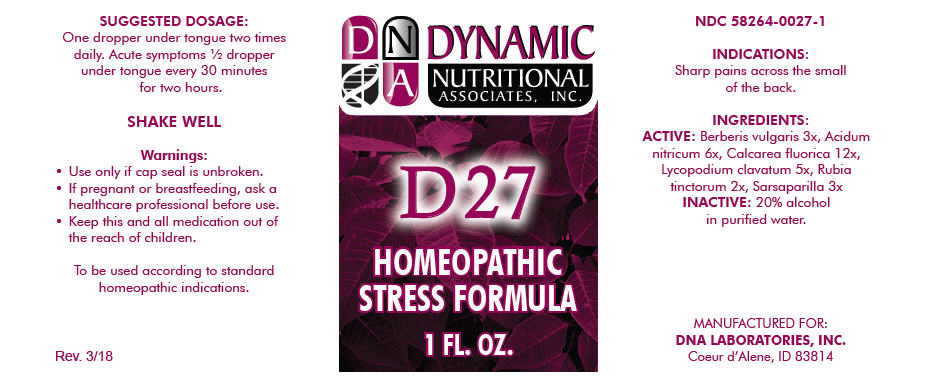 DRUG LABEL: D-27
NDC: 58264-0027 | Form: SOLUTION/ DROPS
Manufacturer: DNA Labs, Inc.
Category: homeopathic | Type: HUMAN OTC DRUG LABEL
Date: 20250113

ACTIVE INGREDIENTS: BERBERIS VULGARIS ROOT BARK 3 [hp_X]/1 mL; NITRIC ACID 6 [hp_X]/1 mL; CALCIUM FLUORIDE 12 [hp_X]/1 mL; LYCOPODIUM CLAVATUM SPORE 5 [hp_X]/1 mL; RUBIA TINCTORUM ROOT 2 [hp_X]/1 mL; SMILAX ORNATA ROOT 3 [hp_X]/1 mL
INACTIVE INGREDIENTS: ALCOHOL; WATER

D-27

NDC 58264-0027-1

INDICATIONS

PURPOSE

Sharp pains across the small of the back.

INGREDIENTS

ACTIVE

Berberis vulgaris 3x, Acidum nitricum 6x, Calcarea fluorica 12x, Lycopodium clavatum 5x, Rubia tinctorum 2x, Sarsaparilla 3x

INACTIVE

20% alcohol in purified water.

SUGGESTED DOSAGE

One dropper under tongue two times daily. Acute symptoms ½ dropper under tongue every 30 minutes for two hours.

STORAGE AND HANDLING

SHAKE WELL

Warnings

- Use only if cap seal is unbroken.

PREGNANCY OR BREAST FEEDING

- If pregnant or breastfeeding, ask a healthcare professional before use.

KEEP OUT OF REACH OF CHILDREN

- Keep this and all medication out of the reach of children.

To be used according to standard homeopathic indications.

PRINCIPAL DISPLAY PANEL - 1 FL. OZ. Bottle Label

DYNAMIC
NUTRITIONAL
ASSOCIATES, INC.

D 27

HOMEOPATHIC
STRESS FORMULA

1 FL. OZ.